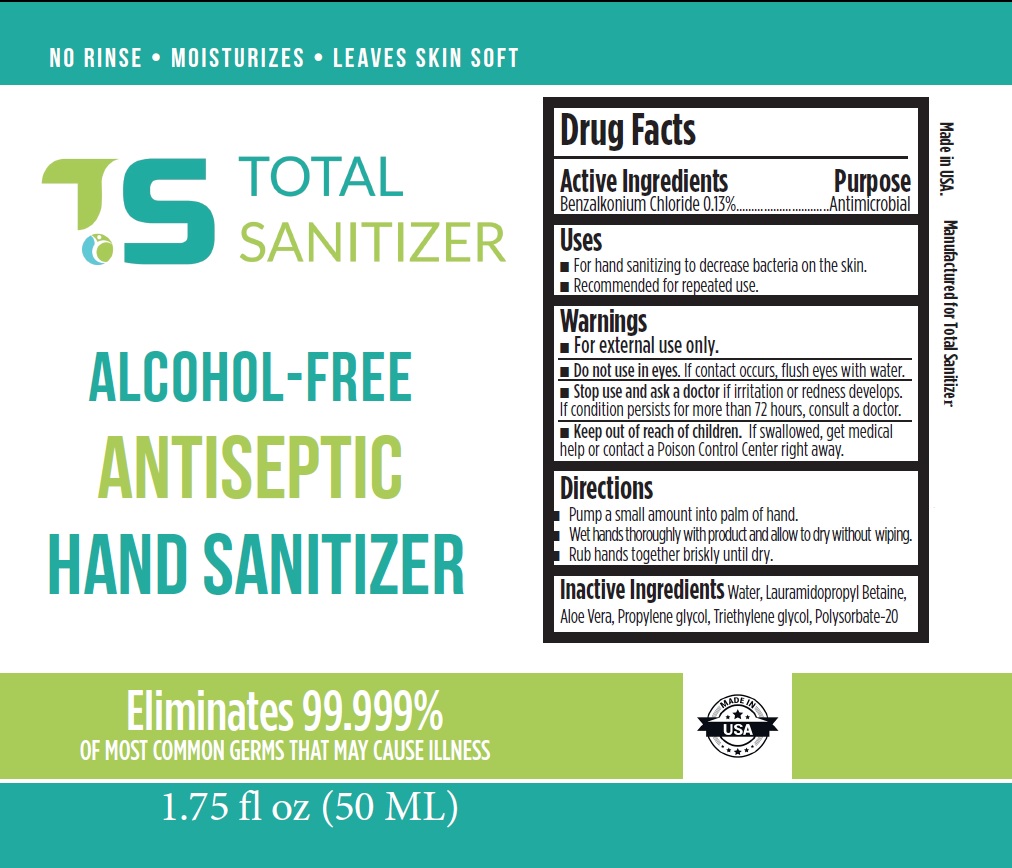 DRUG LABEL: Total Sanitizer Alcohol Free Antiseptic Hand Sanitizer
NDC: 80463-004 | Form: LIQUID
Manufacturer: Total Sanitizer, LLC
Category: otc | Type: HUMAN OTC DRUG LABEL
Date: 20210216

ACTIVE INGREDIENTS: BENZALKONIUM CHLORIDE 1.3 mg/1 mL
INACTIVE INGREDIENTS: WATER; LAURAMIDOPROPYL BETAINE; ALOE VERA LEAF; PROPYLENE GLYCOL; TRIETHYLENE GLYCOL; POLYSORBATE 20

Total Sanitizer Alcohol-Free Antiseptic Hand Sanitizer

Active Ingredients

Benzalkonium Chloride 0.13%

Purpose

Antimicrobial

Uses

- For hand sanitizing to decrease bacteria on the skin.
- Recommended for repeated use.

Warnings

For external use only.

Do not use

in eyes. If contact occurs, flush eyes with water.

Stop use and ask a doctor

if irritation or redness develops. If condition persists for more than 72 hours, consult a doctor.

Keep out of reach of children.

If swallowed, get medical help or contact a Poison Control Center right away.

Directions

- Pump a small amount into palm of hand.
- Wet hands thoroughly with product and allow to dry without wiping.
- Rub hands together briskly until dry.

Inactive Ingredients

Water, Lauramidopropyl Betaine, Aloe Vera, Propylene glycol, Triethylene glycol, Polysorbate-20